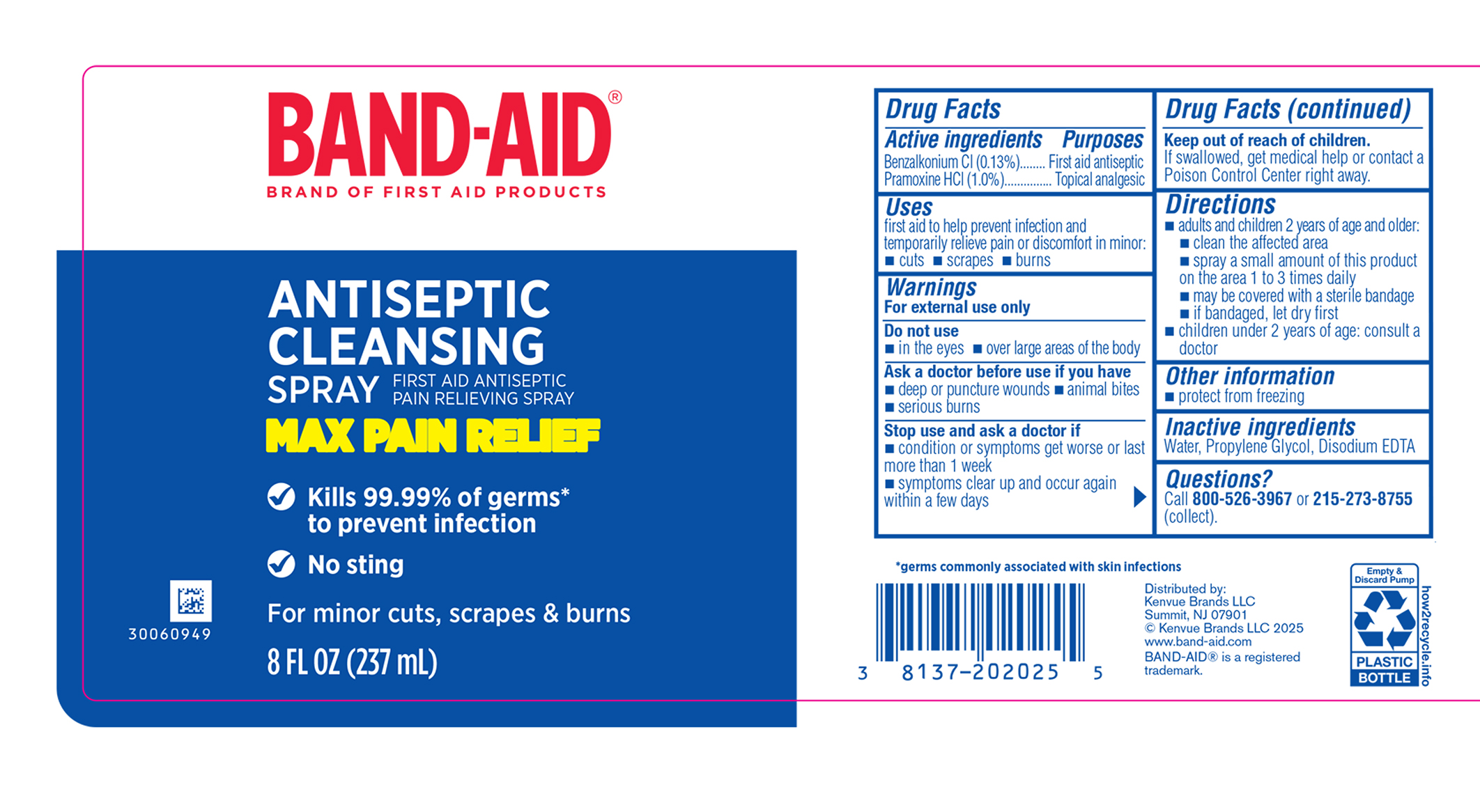 DRUG LABEL: Band Aid Antiseptic Cleansing
NDC: 69968-0729 | Form: SPRAY
Manufacturer: Kenvue Brands LLC
Category: otc | Type: HUMAN OTC DRUG LABEL
Date: 20250605

ACTIVE INGREDIENTS: PRAMOXINE HYDROCHLORIDE 10 mg/1 mL; BENZALKONIUM CHLORIDE 1.3 mg/1 mL
INACTIVE INGREDIENTS: WATER; EDETATE DISODIUM; PROPYLENE GLYCOL

Band Aid Antiseptic Cleansing

Drug Facts

Active ingredients

Benzalkonium Cl (0.13%)

Pramoxine HCl (1.0%)

Purposes

First aid antiseptic

Topical analgesic

Use

Uses

first aid to help prevent infection

and temporarily relieve pain or discomfort in minor:

•cuts •scrapes •burns

Warnings

- For external use only.

Do not use

· in the eyes • over large areas of the body

Ask a doctor before use if you have

- deep or puncture wounds · animal bites
- serious burns

Stop use and ask a doctor if

- condition or symptoms get worse or last more than 1 week
- symptoms clear up and occur again within a few days

Keep out of reach of children.

If swallowed, get medical help or contact a Poison Control Center right away.

Directions

- adults and children 2 years of age and older:
- clean the affected area
- spray a small amount of this product on the area 1 to 3 times daily
- may be covered with a sterile bandage
- if bandaged, let dry first
- children under 2 years of age: consult a doctor

Other information

protect from freezing

Inactive ingredients

Water, Propylene Glycol, Disodium EDTA

Questions?

call 800-526-3967 or 215-273-8755 (collect).

Distributed by:
Kenvue Brands LLC
Summit, NJ 07901

PRINCIPAL DISPLAY PANEL - 237 mL Bottle

BAND-AID®

BRAND OF FIRST AID PRODUCTS

ANTISEPTIC

CLEANSING

SPRAY

FIRST AID ANTISEPTIC

PAIN RELEIVING SPRAY

MAX PAIN RELIEF

Kills 99.99% of germs*

to prevent infection

No sting

For minor cuts, scrapes & burns

8 FL OZ (237mL)